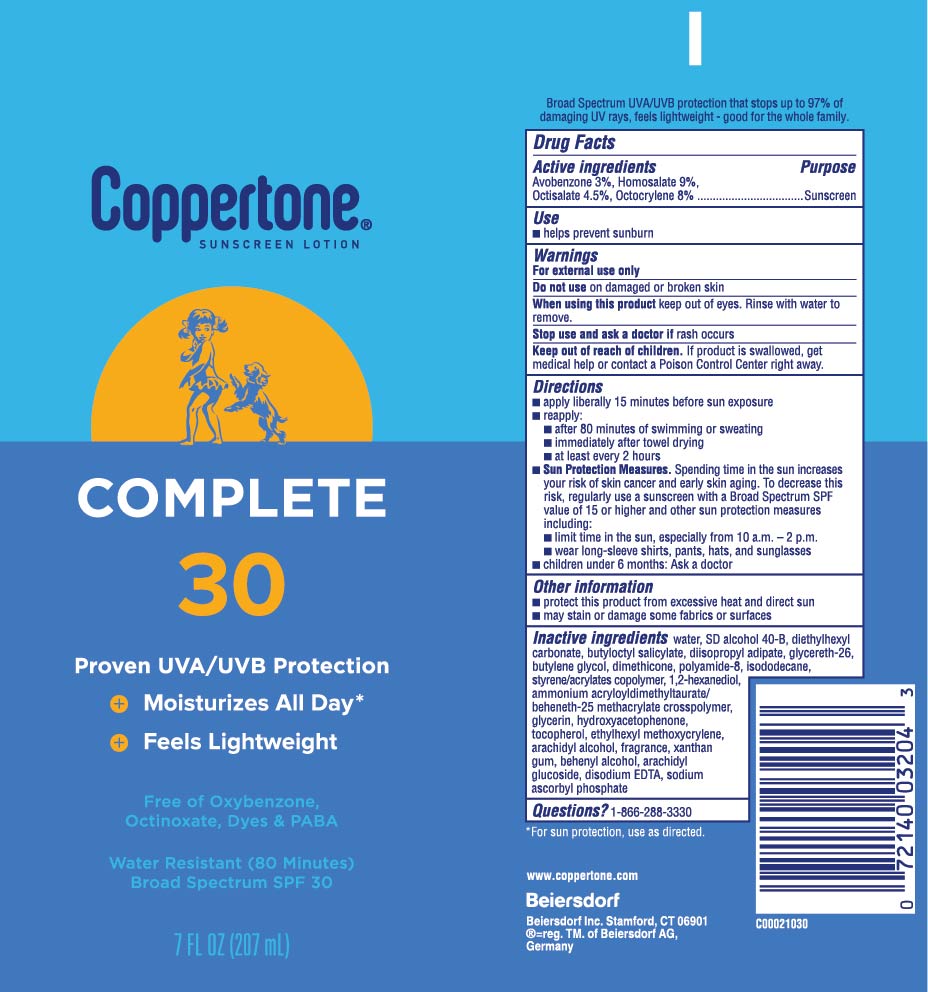 DRUG LABEL: Coppertone Complete Sunscreen SPF 30
NDC: 66800-0026 | Form: LOTION
Manufacturer: Beiersdorf Inc
Category: otc | Type: HUMAN OTC DRUG LABEL
Date: 20251231

ACTIVE INGREDIENTS: AVOBENZONE 3 g/100 g; OCTOCRYLENE 8 g/100 g; OCTISALATE 4.5 g/100 g; HOMOSALATE 9 g/100 g
INACTIVE INGREDIENTS: DIISOPROPYL ADIPATE; GLYCERETH-26; BUTYLENE GLYCOL; POLYAMIDE-8 (4500 MW); ISODODECANE; 1,2-HEXANEDIOL; GLYCERIN; HYDROXYACETOPHENONE; TOCOPHEROL; ARACHIDYL ALCOHOL; FRAGRANCE FRESH CITRUS FLORAL ORC1501495; XANTHAN GUM; DOCOSANOL; ARACHIDYL GLUCOSIDE; SODIUM ASCORBYL PHOSPHATE; DISODIUM EDTA-COPPER; AMMONIUM ACRYLOYLDIMETHYLTAURATE/BEHENETH-25 METHACRYLATE CROSSPOLYMER (52000 MPA.S); BUTYLOCTYL SALICYLATE; DIMETHICONE; STYRENE/ACRYLAMIDE COPOLYMER (MW 500000); ETHYLHEXYL METHOXYCRYLENE; DIETHYLHEXYL CARBONATE; WATER; ALCOHOL

Complete Lotion SPF 30

Active ingredients

Avobenzone 3%, Homosalate 9%, Octisalate 4.5%, Octocrylene 8%

Purpose

Sunscreen

Uses

■ helps prevent sunburn

■ if used as directed with other sun protection measures (see Directions), decreases the risk of skin cancer and early skin aging caused by the sun

Warnings

For external use only

Do not useon damaged or broken skin

WHEN USING

When using this productkeep out of eyes. Rinse with water to remove.

Stop use and ask a doctor ifrash occurs

Keep out of reach of children.If product is swallowed, get medical help or contact a Poison Control Center right away.

Directions

■ apply liberally 15 minutes before sun exposure

■ reapply:

■ after 80 minutes of swimming or sweating

■ immediately after towel drying

■ at least every 2 hours

■ Sun Protection Measures.Spending time in the sun increases your risk of skin cancer and early skin aging. To decrease this risk, regularly use a sunscreen with a Broad Spectrum SPF value of 15 or higher and other sun protection measures including:

■ limit time in the sun, especially from 10 a.m. – 2 p.m.

■ wear long-sleeve shirts, pants, hats, and sunglasses

■ children under 6 months: Ask a doctor

Other information

■ protect this product from excessive heat and direct sun

■ may stain or damage some fabrics or surfaces

Inactive ingredients

water, SD alcohol 40-B, diethylhexyl carbonate, butyloctyl salicylate, diisopropyl adipate, glycereth-26, butylene glycol, dimethicone, polyamide-8, isododecane, styrene/acrylates copolymer, 1,2-hexanediol, ammonium acryloyldimethyltaurate/beheneth-25 methacrylate crosspolymer, glycerin, hydroxyacetophenone, tocopherol, ethylhexyl methoxycrylene, arachidyl alcohol, fragrance, xanthan gum, behenyl alcohol, arachidyl glucoside, disodium EDTA, sodium ascorbyl phosphate

Questions?

1-866-288-3330

PACKAGE LABEL

Coppertone®Sunscreen Lotion

Complete 30

Proven UVA/UVB Protection

+ Moisturizes All Day*

+ Feels Lightweight

Free of Oxybenzone, Octinoxate, Dyes & PABA

Water Resistant (80 Minutes)

Broad Spectrum SPF 30